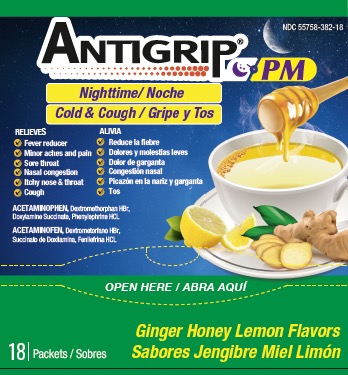 DRUG LABEL: ANTIGRIP
NDC: 55758-382 | Form: POWDER, FOR SOLUTION
Manufacturer: Pharmadel LLC
Category: otc | Type: HUMAN OTC DRUG LABEL
Date: 20240327

ACTIVE INGREDIENTS: DOXYLAMINE SUCCINATE 6.25 mg/1 1; ACETAMINOPHEN 325 mg/1 1; DEXTROMETHORPHAN HYDROBROMIDE 10 mg/1 1; PHENYLEPHRINE HYDROCHLORIDE 5 mg/1 1
INACTIVE INGREDIENTS: ANHYDROUS CITRIC ACID; ISOPROPYL ALCOHOL; MALTODEXTRIN; WATER; SILICON DIOXIDE; ACESULFAME POTASSIUM; ASPARTAME; SODIUM CITRATE; SUCROSE; TRIBASIC CALCIUM PHOSPHATE

Antigrip Nighttime Tea G-H-L (AS)

Active Ingredients & Purposes

PURPOSE

Active ingredients (in each packet) | Purposes
Acetaminophen 325 mg………………………………… | Pain reliever/ fever reducer
Dextromethorphan HBr 10 mg…………………………... | Cough suppressant
Doxylamine succinate 6.25 mg ..................................... | Antihistamine
Phenylephrine HCI 5 mg…….………………………….. | Nasal decongestant

Uses

Temporary relieves common cold/flu symptoms:

- minor aches and pains
- sore throat
- headache
- nasal congestion
- runny nose

- itching of nose or throat
- stuffy nose
- cough due to minor throat and bronchial irritation
- and temporarily reduces fever

Warnings

Liver Warning: This product contains acetaminophen. Severe liver damage may occur if you take

- more than 6 packets in 24 hours, which is the maximum daily amount for this product
- with other drugs containing acetaminophen
- 3 or more alcoholic drinks every day while using this product

Sore throat warning: if sore throat is severe, persists for more than 2 days, is accompanied or followed by fever, headache, rash, nausea, or vomiting, consult a doctor promptly.

Do not use

- with any other drug containing acetaminophen (prescription or nonprescription). If you are not sure whether a drug contains acetaminophen, ask a doctor or pharmacist.
- if you are now taking prescription monoamine oxidase inhibitor (MAOI) (certain drugs for depression, psychiatric, or emotional conditions, or Parkinson's disease), or 2 weeks after stopping the MAOI drug. If you do not know if your prescription drug contains an MAOI, ask a doctor or pharmacist before taking this product

Ask a doctor before use if you

- have liver disease
- have heart disease
- have high blood pressure
- have thyroid disease
- have diabetes
- have glaucoma
- have a cough that is accompanied by excessive phlegm (mucus)
- have a persistent or chronic cough such as occurs with smoking, asthma, chronic bronchitis, or emphysema
- have difficulty urinating due to an enlarged prostate gland
- are taking sedatives or tranquilizers

Ask a doctor or pharmacist before use if you are

- taking the blood thinning drug warfarin

When using this product

- do not exceed recommended dosage
- may cause excitability, especially in children
- use caution when driving a motor vehicle or operating machinery
- may cause marked drowsiness

Stop use and ask doctor if

- nervousness, dizziness, or sleeplessness occurs
- redness or swelling is present
- pain, cough, or nasal congestion gets worse or lasts more than 7 days
- fever gets worse or lasts more than 3 days
- any new symptoms occur
- cough comes back or occurs with rash or headache that lasts.

These could be signs of a serious condition.

If pregnant or breast-feeding,

ask a health professional before use.

KEEP OUT OF REACH OF CHILDREN.

In case of an accidental overdose, get medical help or contact a Poison Control Center right away. Prompt medical attention is critical for adults as well as for children even if you do not notice any signs or symptoms.

Directions

- dissolve one packet in an 8oz. glass of hot water. If using a microwave; add content into a glass of cool water and stir briskly before and after heating. Do not overheat.
- sip while hot and consume the entire drink within 10-15 minutes

Age | Dose
adults and children 12 years of age and over | one (1) packet every 4 hours,; take every 4 hours; do not exceed 6 packets in a 24 hours
children under 12 years of age | do not use

Other information

- each packet contains: potassium 10 mg, sodium 27 mg
- phenylketonurics: contains phenylalanine 13 mg per packet
- store at room temperature 68-77°F (20-25°C)
- do not use if packet is punctured or torn

Inactive ingredients

acesulfame potassium, anhydrous citric acid, aspartame, isopropyl alcohol, lemon ginger honey flavors, maltodextrin, silicon dioxide, sodium citrate, sucrose, tribasic calcium phosphate, water

Questions & comments?

1-866-359-3478 (M-F) 9 AM to 5 PM EST or www.pharmadel.com

Dist by:

PHARMADEL LLC

New Castle, DE 19720